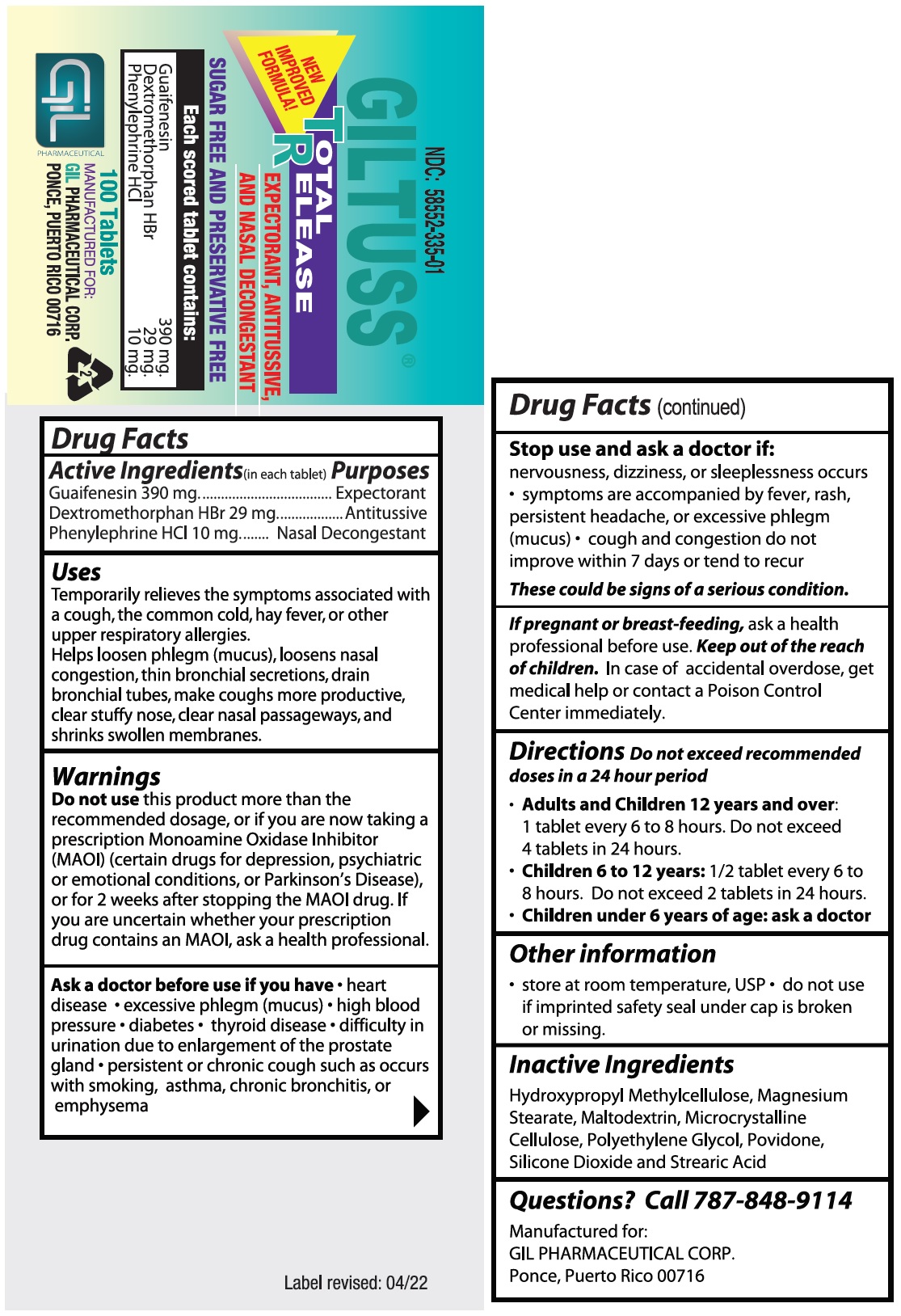 DRUG LABEL: Giltuss TR
NDC: 58552-335 | Form: TABLET
Manufacturer: Gil Pharmaceutical Corp
Category: otc | Type: HUMAN OTC DRUG LABEL
Date: 20251009

ACTIVE INGREDIENTS: GUAIFENESIN 390 mg/1 1; DEXTROMETHORPHAN HYDROBROMIDE 29 mg/1 1; PHENYLEPHRINE HYDROCHLORIDE 10 mg/1 1
INACTIVE INGREDIENTS: HYPROMELLOSE, UNSPECIFIED; MAGNESIUM STEARATE; MALTODEXTRIN; MICROCRYSTALLINE CELLULOSE; POLYETHYLENE GLYCOL, UNSPECIFIED; POVIDONE; SILICON DIOXIDE; STEARIC ACID

GILTUSS®TOTAL RELEASE
EXPECTORANT, ANTITUSSIVE AND NASAL DECONGESTANT>
SUGAR FREE AND PRESERVATIVE FREE

Drug Facts

Active Ingredients(in each tablet)

Guaifenesin 390 mg.

Dextromethorphan HBr 29 mg.

Phenylephrine HCl 10 mg.

Purposes

Expectorant

Antitussive

Nasal Decongestant

Uses

Temporarily relieves the symptoms associated with a cough, the common cold, hay fever, or other upper respiratory allergies.

Helps loosen phlegm (mucus), loosens nasal congestion, thin bronchial secretions, drain bronchial tubes, make coughs more productive, clear stuffy nose, clear nasal passageways, and shrinks swollen membranes.

Warnings

Do not usethis product more than the recommended dosage, or if you are now taking a prescription Monoamine Oxidase Inhibitor (MAOI) (certain drugs for depression, psychiatric or emotional conditions, or Parkinson’s Disease), or for 2 weeks after stopping the MAOI drug.

If you are uncertain whether your prescription drug contains an MAOI, ask a health professional.

Ask a doctor before use if you have

• heart disease.

• excessive phlegm (mucus).

• high blood pressure.

• diabetes.

• thyroid disease.

• difficulty in urination due to enlargement of the prostate gland.

• persistent or chronic cough such as occurs with smoking, asthma, chronic bronchitis, or emphysema.

Stop use and ask a doctor if:

• nervousness, dizziness, or sleeplessness occurs.

• symptoms are accompanied by fever, rash, persistent headache, or excessive phlegm (mucus).

• cough and congestion do not improve within 7 days or tend to recur.

These could be signs of a serious condition.

PREGNANCY OR BREAST FEEDING

If pregnant or breast-feeding,ask a health professional before use . Keep out of the reach of children. In case of accidental overdose, get medical help or contact a Poison Control Center immediately.

Directions

Do not exceed recommended doses in a 24 hour period

- Adults and Children 12 years and over:1 tablet every 6 to 8 hours. Do not exceed 4 tablets in 24 hours.
- Children 6 to 12 years:1/2 tablet every 6 to 8 hours. Do not exceed 2 tablets in 24 hours.
- Children under 6 years of age: ask a doctor.

Other information

• store at room temperature, USP.

• do not use if imprinted safety seal under cap is broken or missing.

Inactive Ingredients

Hydroxypropyl Methylcellulose, Magnesium Stearate, Maltodextrin, Microcrystalline Cellulose, Polyethylene Glycol, Povidone, Silicone Dioxide and Stearic Acid.

Questions? Call 787-848-9114

Manufactured for:

GIL PHARMACEUTICAL CORP.

Ponce, Puerto Rico 00716

Label revised: 04/22

PACKAGE LABEL.PRINCIPAL DISPLAY PANEL

Giltuss®Total Release - NDC-58552-335-01 - 100's Bottle Label.